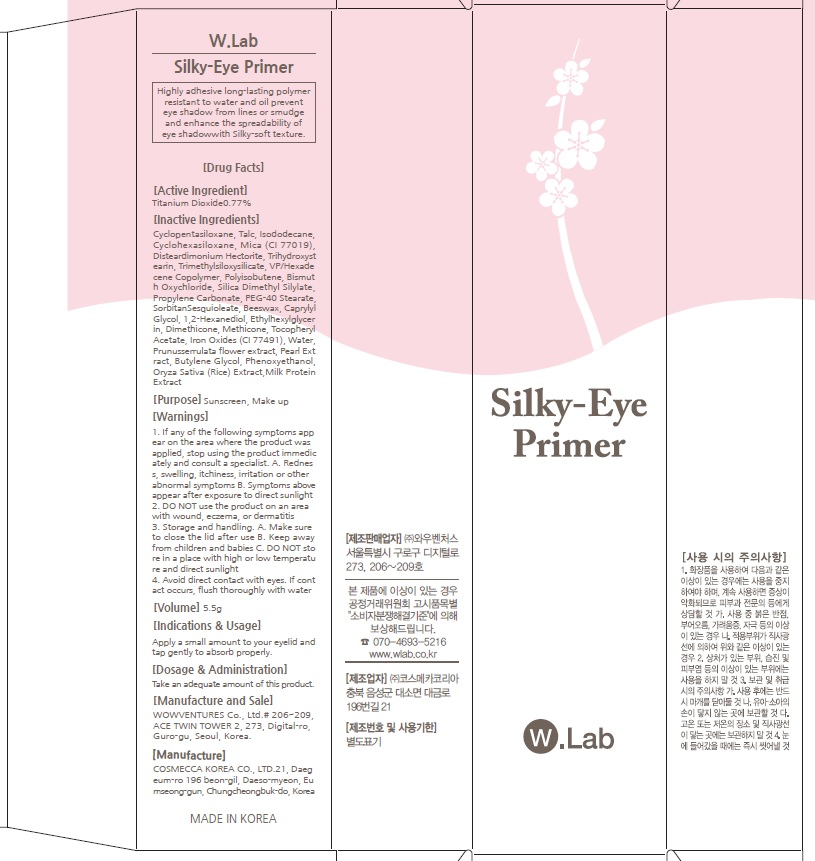 DRUG LABEL: Silky Eye Primer
NDC: 69894-330 | Form: CREAM
Manufacturer: WOW VENTURES
Category: otc | Type: HUMAN OTC DRUG LABEL
Date: 20151208

ACTIVE INGREDIENTS: Titanium Dioxide 0.04 g/5.5 g
INACTIVE INGREDIENTS: Talc; Isododecane

ACTIVE INGREDIENT

Active Ingredient: Titanium Dioxide 0.77%

INACTIVE INGREDIENT

Inactive Ingredients: Cyclopentasiloxane, Talc, Isododecane, Cyclohexasiloxane, Mica (CI 77019), DisteardimoniumHectorite, Trihydroxystearin, Trimethylsiloxysilicate, VP/Hexadecene Copolymer, Polyisobutene, Bismuth Oxychloride, Silica Dimethyl Silylate, Propylene Carbonate, PEG-40 Stearate, SorbitanSesquioleate, Beeswax, Caprylyl Glycol, 1,2-Hexanediol, Ethylhexylglycerin, Dimethicone, Methicone, Tocopheryl Acetate, Iron Oxides (CI 77491), Water, Prunusserrulata flower extract, Pearl Extract, Butylene Glycol, Phenoxyethanol, Oryza Sativa (Rice) Extract, Milk Protein Extract

PURPOSE

Purpose: Sunscreen, Make up

WARNINGS

Warnings: 1. If any of the following symptoms appear on the area where the product was applied, stop using the product immediately and consult a specialist. A. Redness, swelling, itchiness, irritation or other abnormal symptoms B. Symptoms above appear after exposure to direct sunlight 2. DO NOT use the product on an area with wound, eczema, or dermatitis 3. Storage and handling. A. Make sure to close the lid after use B. Keep away from children and babies C. DO NOT store in a place with high or low temperature and direct sunlight 4. Avoid direct contact with eyes. If contact occurs, flush thoroughly with water

DESCRIPTION

Indications & Usage: Apply a suitable amount to your eyelid.

Dosage & Administration: Take an adequate amount of this product.